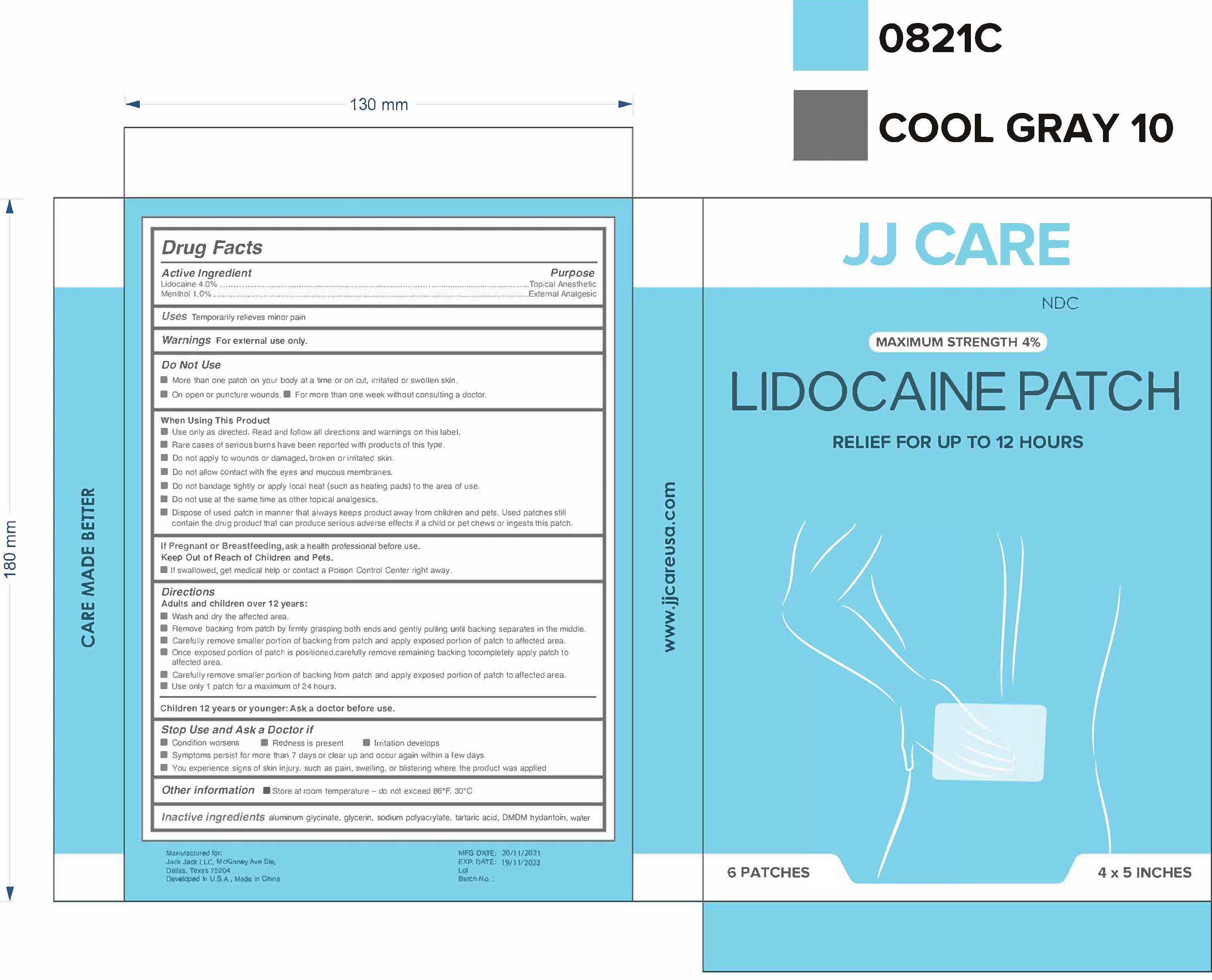 DRUG LABEL: Lidocaine Patch
NDC: 81484-301 | Form: PATCH
Manufacturer: Anhui Miao De Tang Pharmaceutical Co., Ltd.
Category: otc | Type: HUMAN OTC DRUG LABEL
Date: 20231114

ACTIVE INGREDIENTS: MENTHOL 0.1 g/1 1; LIDOCAINE 0.4 g/1 1
INACTIVE INGREDIENTS: GLYCERIN; DMDM HYDANTOIN; TARTARIC ACID; SODIUM POLYACRYLATE (2500000 MW); DIHYDROXYALUMINUM AMINOACETATE; WATER

Lidocaine Patch

LIDOCAINE PATCH

Active Ingredient(s)

LIDOCAINE 4% Purpose:Topical Analgesic

MENTHOL 1% Purpose: External Analges

Purpose

Topical Anesthetic, External Analges, LIDOCAINE PATCH

Use

LIDOCAINE PATCH to help Temporarily relteves minor pain

Warnings

For external use only. Flammable.

Do not use

• More than one patch on your body at a time or on cut, irritated or swollen skin
• On open or puncture wounds

• For more than one week without consulling a doctor.

WHEN USING

• Use only as directed. Read and邸ow all directions and warnings on this label.
• Rare cases of serious burns have been reported with products of this type.
• Oo not apply to wou心s or damaged, broken or irritated skin
• Do not allow contact with the eyes and mucous membranes.
• Do not bandage tightly or apply local heat (such as heating pads) to the area of use
• Do not use at the same time as other topical analgesics.
• Dispose of used patch in manner that always keeps producl away from children and pets. Used patches still contain the drug product that can produce serious adverse effects if a child or pet chews or ingests this patch.

Stop use and ask a doctor if irritation or rash occurs. These may be signs of a serious condition.

Keep out of reach of children. If swallowed, get medical help or contact a Poison Control Center right away.

Directions

Adults and children over 12 years:

• Wash and dry the affected area.
• Remove backing from patch by firmty grasping both ends and gently pulling until backing separates in the middle

• Carefully remove smaller portion of back,ng from patch and apply exposed portion of patch to a什ected area
• Once exposed portion of patch is po奾oned.carefully remove remaining backing tocomplelely apply patch to affected area.
• Carefully remove smaller portion of backing from patch and apply exposed portion of patch to affected area
• Use only 1 patch for a maximum of 24 hours.

Other information

- Store at room temperature - do not exceed 86'F, 30'C

Inactive ingredients

aluminum glycinate, glycerin, sodium polyacrylate. tartaric acid, DMOM hydantoin, water